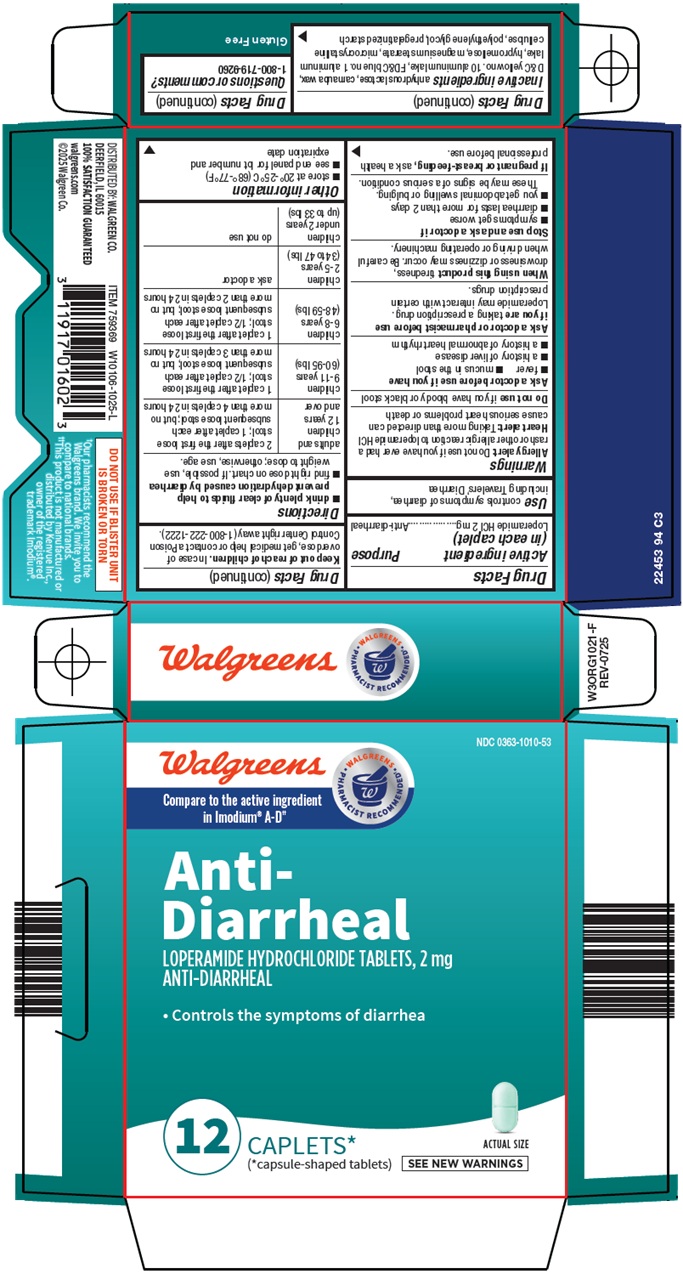 DRUG LABEL: anti diarrheal
NDC: 0363-1010 | Form: TABLET, FILM COATED
Manufacturer: Walgreen Company
Category: otc | Type: HUMAN OTC DRUG LABEL
Date: 20260301

ACTIVE INGREDIENTS: LOPERAMIDE HYDROCHLORIDE 2 mg/1 1
INACTIVE INGREDIENTS: ANHYDROUS LACTOSE; CARNAUBA WAX; D&C YELLOW NO. 10 ALUMINUM LAKE; FD&C BLUE NO. 1 ALUMINUM LAKE; HYPROMELLOSE, UNSPECIFIED; MAGNESIUM STEARATE; MICROCRYSTALLINE CELLULOSE; POLYETHYLENE GLYCOL, UNSPECIFIED

Walgreen Co. Anti-Diarrheal Drug Facts

Active ingredient (in each caplet)

Loperamide HCl 2 mg

Purpose

Anti-diarrheal

Use

controls symptoms of diarrhea, including Travelers’ Diarrhea

Warnings

Allergy alert: Do not use if you have ever had a rash or other allergic reaction to loperamide HCl

Heart alert: Taking more than directed can cause serious heart problems or death

Do not use

if you have bloody or black stool

Ask a doctor before use if you have

- fever
- mucus in the stool
- a history of liver disease
- a history of abnormal heart rhythm

Ask a doctor or pharmacist before use if you are

taking a prescription drug. Loperamide may interact with certain prescription drugs.

When using this product

tiredness, drowsiness or dizziness may occur. Be careful when driving or operating machinery.

Stop use and ask a doctor if

- symptoms get worse
- diarrhea lasts for more than 2 days
- you get abdominal swelling or bulging. These may be signs of a serious condition.

If pregnant or breast-feeding,

ask a health professional before use.

Keep out of reach of children.

In case of overdose, get medical help or contact a Poison Control Center right away (1-800-222-1222).

Directions

- drink plenty of clear fluids to help prevent dehydration caused by diarrhea
- find right dose on chart. If possible, use weight to dose; otherwise, use age.

adults and children; 12 years and over | 2 caplets after the first loose stool; 1 caplet after each subsequent loose stool; but no more than 4 caplets in 24 hours
children 9-11 years; (60-95 lbs) | 1 caplet after the first loose stool; 1/2 caplet after each subsequent loose stool; but no more than 3 caplets in 24 hours
children 6-8 years; (48-59 lbs) | 1 caplet after the first loose stool; 1/2 caplet after each subsequent loose stool; but no more than 2 caplets in 24 hours
children 2-5 years; (34 to 47 lbs) | ask a doctor
children under 2 years; (up to 33 lbs) | do not use

Other information

- store at 20°-25°C (68°-77°F)
- see end panel for lot number and expiration date

Inactive ingredients

anhydrous lactose, carnauba wax, D&C yellow no. 10 aluminum lake, FD&C blue no. 1 aluminum lake, hypromellose, magnesium stearate, microcrystalline cellulose, polyethylene glycol, pregelatinized starch

Questions or comments?

1-800-719-9260

Principal Display Panel

Walgreens

WALGREENS PHARMACIST RECOMMENDED

Compare to the active ingredient in Imodium® A-D

Anti-Diarrheal

LOPERAMIDE HYDROCHLORIDE TABLETS, 2 mg

ANTI-DIARRHEAL

• Controls the symptoms of diarrhea

12 CAPLETS*

(*capsule-shaped tablets)

ACTUAL SIZE

SEE NEW WARNINGS